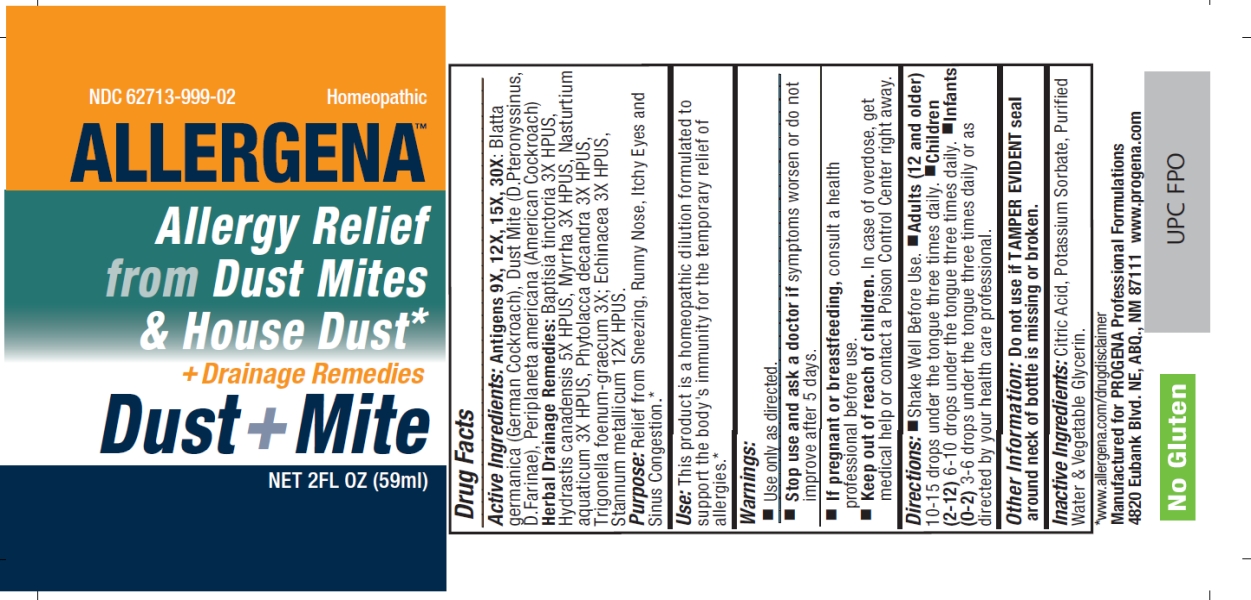 DRUG LABEL: Allergena
NDC: 62713-999 | Form: LIQUID
Manufacturer: Meditrend, Inc. DBA Progena Professional Formulations
Category: homeopathic | Type: HUMAN OTC DRUG LABEL
Date: 20240619

ACTIVE INGREDIENTS: ECHINACEA, UNSPECIFIED 3 [hp_X]/1 mL; BAPTISIA TINCTORIA ROOT 3 [hp_X]/1 mL; GOLDENSEAL 3 [hp_X]/1 mL; MYRRH 3 [hp_X]/1 mL; NASTURTIUM OFFICINALE 3 [hp_X]/1 mL; PHYTOLACCA AMERICANA ROOT 3 [hp_X]/1 mL; FENUGREEK LEAF 3 [hp_X]/1 mL; BLATTELLA GERMANICA 30 [hp_X]/1 mL; DERMATOPHAGOIDES PTERONYSSINUS 30 [hp_X]/1 mL; DERMATOPHAGOIDES FARINAE 30 [hp_X]/1 mL; PERIPLANETA AMERICANA 30 [hp_X]/1 mL; TIN 12 [hp_X]/1 mL
INACTIVE INGREDIENTS: WATER; CITRIC ACID ACETATE; POTASSIUM SORBATE; GLYCERIN

Dust + Mite

ACTIVE INGREDIENT

Active Ingredients: Antigens 9X, 12X, 15X, 30X: Blatta Germanica (German Cockroach) HPUS, Dust Mite (D.Pteronyssinus, D. Farinae), Periplaneta Americana (American Cockroach) HPUS; Herbal Drainage Remedies 3X: Baptisia Tinctoria HPUS, Hydrastis Canadensis HPUS, Myrrha HPUS, Nasturtium Aquaticum HPUS, Phytolacca Decandra HPUS, Trigonella Foenum-Graecum;Echinacea 3X HPUS, Stannum Metallicum 12X HPUS.

PURPOSE

Purpose:Relief from Sneezing, Runny Nose, Itchy Eyes and Sinus Congestion.*

INDICATIONS AND USAGE

Use:This product is a Homeopathic Dilution formulated to support the body's immunity for the temporary relief of allergies.*

Keep Out of Reach of Children.In case of overdose, get medical help or contact a Poison Control Center right away.

Warnings:

- Use Only as directed.
- Stop use and ask a doctor if symptoms worsen or do not improve after 5 days.
- If pregnant or breast-feeding, consult a health care professional before use.

DOSAGE AND ADMINISTRATION

Directions:• Shake Well Before Use.• Adults (12 and Older)10-15 drops under the tongue three times daily.• Children (2-12) 6-10 drops under the tongue three times daily. • Infants (0-2)3-6 drops under the tongue three times daily or as directed by your health care professional.

Other Information: Do not use if TAMPER EVIDENT seal around neck of bottle is missing or broken.

INACTIVE INGREDIENT

Inactive Ingredients:Citric Acid, Potassium Sorbate, Purified Water & Vegetable Glycerin.

PACKAGE LABEL

*www.allergena.com/drugdisclaimer

Manufacturedfor Progena Professional Formulations

4820 Eubank Blvd. NE, ABQ, NM 87111, www.allergena.com